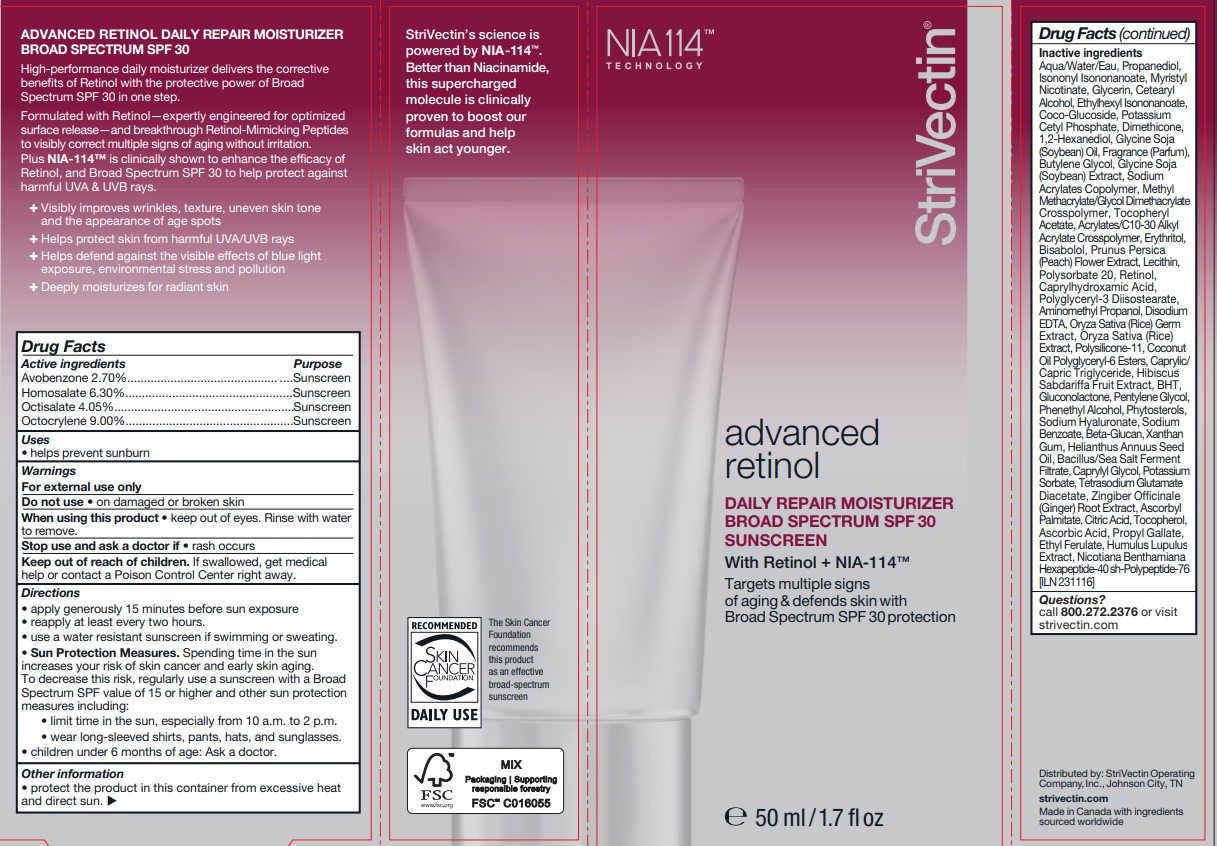 DRUG LABEL: StriVectin Advanced Retinol Daily Repair Moisturizer
NDC: 76147-236 | Form: LOTION
Manufacturer: StriVectin Operating Company, Inc.
Category: otc | Type: HUMAN OTC DRUG LABEL
Date: 20251209

ACTIVE INGREDIENTS: AVOBENZONE 2.7 g/100 mL; OCTISALATE 4.05 g/100 mL; OCTOCRYLENE 9 g/100 mL; HOMOSALATE 6.3 g/100 mL
INACTIVE INGREDIENTS: .ALPHA.-TOCOPHEROL ACETATE; ERYTHRITOL; XANTHAN GUM; PHENYLETHYL ALCOHOL; SODIUM BENZOATE; METHYL METHACRYLATE/GLYCOL DIMETHACRYLATE CROSSPOLYMER; WATER; PROPANEDIOL; ISONONYL ISONONANOATE; MYRISTYL NICOTINATE; GLYCERIN; ETHYLHEXYL ISONONANOATE; COCO GLUCOSIDE; POTASSIUM CETYL PHOSPHATE; PRUNUS PERSICA FLOWER; RETINOL; YEAST .BETA.-D-GLUCAN; ZINGIBER OFFICINALE (GINGER) ROOT OIL; TOCOPHEROL; .BETA.-SITOSTEROL; HIBISCUS SABDARIFFA WHOLE; ORYZA SATIVA (RICE) GERM POWDER; GLYCINE SOJA (SOYBEAN) OIL UNSAPONIFIABLES; ORYZA SATIVA WHOLE; DIMETHICONE; HYALURONATE SODIUM; GLUCONOLACTONE; POLYGLYCERYL-3 DIISOSTEARATE; SOYBEAN OIL; ASCORBYL PALMITATE; ASCORBIC ACID; POLYSORBATE 20; COCONUT OIL GLYCERETH-8 ESTERS; POTASSIUM SORBATE; BUTYLATED HYDROXYTOLUENE; PENTYLENE GLYCOL; BUTYLENE GLYCOL; LECITHIN, SOYBEAN; PROPYL GALLATE; AMINOMETHYLPROPANOL; CAPRYLYL GLYCOL; SODIUM ACRYLATE; 1,2-HEXANEDIOL; TETRASODIUM GLUTAMATE DIACETATE; EDETATE DISODIUM; ANHYDROUS CITRIC ACID; ACRYLATES/C10-30 ALKYL ACRYLATE CROSSPOLYMER (60000 MPA.S); ETHYL FERULATE; NICOTIANA BENTHAMIANA WHOLE; CAPRYLIC/CAPRIC TRIGLYCERIDE; HELIANTHUS ANNUUS (SUNFLOWER) SEED OIL; CETEARYL ALCOHOL; HUMULUS LUPULUS WHOLE; BISABOLOL; CAPRYLHYDROXAMIC ACID; FRAGRANCE CUCUMBER ALOE ORC1802955

StriVectin - Advanced Retinol Daily Repair Moisturizer Broad Spectrum SPF30

Active Ingredients

Avobenzone 2.70%
Homosalate 6.30%
Octisalate 4.05%
Octocrylene 9.00%

Purpose

Sunscreen

Warnings

• For external use only
• Do not useon damaged or broken skin
• When using this productkeep out of eyes. Rinse with water to remove.
• Stop use and ask a doctor ifrash occurs

Keep out of reach of children. If swallowed, get medical help or contact a Poison Control Center right away.

USES

- helps prevent sunburn
- if used as directed with other sun protection measures (see Directions), decreases the risk of skin cancer and early skin aging caused by the sun

Other information

Protect the product in this container from excessive heat and direct sun.

Directions

- Apply generously 15 minutes before sun exposure and as needed
- Reapply at least every two hours.
- Use a water resistant sunscreen if swimming or sweating.

Sun Protection Measures. Spending time in the sun increases your risk of skin cancer and early skin aging. To decrease this risk, regularly use a sunscreen with a Broad Spectrum SPF value of 15 or higher and other sun protection measures including:

- limit time in the sun, especially from 10 a.m. to 2 p.m.
- wear long-sleeved shirts, pants, hats, and sunglasses.
- Children under 6 months of age: Ask a doctor.

Inactive Ingredients

Aqua/Water/Eau, Propanediol, Isononyl Isononanoate, Myristyl Nicotinate, Glycerin, Cetearyl Alcohol, Ethylhexyl Isononanoate, Coco-Glucoside, Potassium Cetyl Phosphate, Dimethicone, 1,2-Hexanediol, Glycine Soja (Soybean) Oil, Fragrance (Parfum), Butylene Glycol, Glycine Soja (Soybean) Extract, Sodium Acrylates Copolymer, Methyl Methacrylate/Glycol Dimethacrylate Crosspolymer, Tocopheryl Acetate, Acrylates/C10-30 Alkyl Acrylate Crosspolymer, Erythritol, Bisabolol, Prunus Persica (Peach) Flower Extract, Lecithin, Polysorbate 20, Retinol, Caprylhydroxamic Acid, Polyglyceryl-3 Diisostearate, Aminomethyl Propanol, Disodium EDTA, Oryza Sativa (Rice) Germ Extract, Oryza Sativa (Rice) Extract, Polysilicone-11, Coconut Oil Polyglyceryl-6 Esters, Caprylic/ Capric Triglyceride, Hibiscus Sabdariffa Fruit Extract, BHT, Gluconolactone, Pentylene Glycol, Phenethyl Alcohol, Phytosterols, Sodium Hyaluronate, Sodium Benzoate, Beta-Glucan, Xanthan Gum, Helianthus Annuus Seed Oil, Bacillus/Sea Salt Ferment Filtrate, Caprylyl Glycol, Potassium Sorbate, Tetrasodium Glutamate Diacetate, Zingiber Officinale (Ginger) Root Extract, Ascorbyl Palmitate, Citric Acid, Tocopherol, Ascorbic Acid, Propyl Gallate, Ethyl Ferulate, Humulus Lupulus Extract, Nicotiana Benthamiana Hexapeptide-40 sh-Polypeptide-76